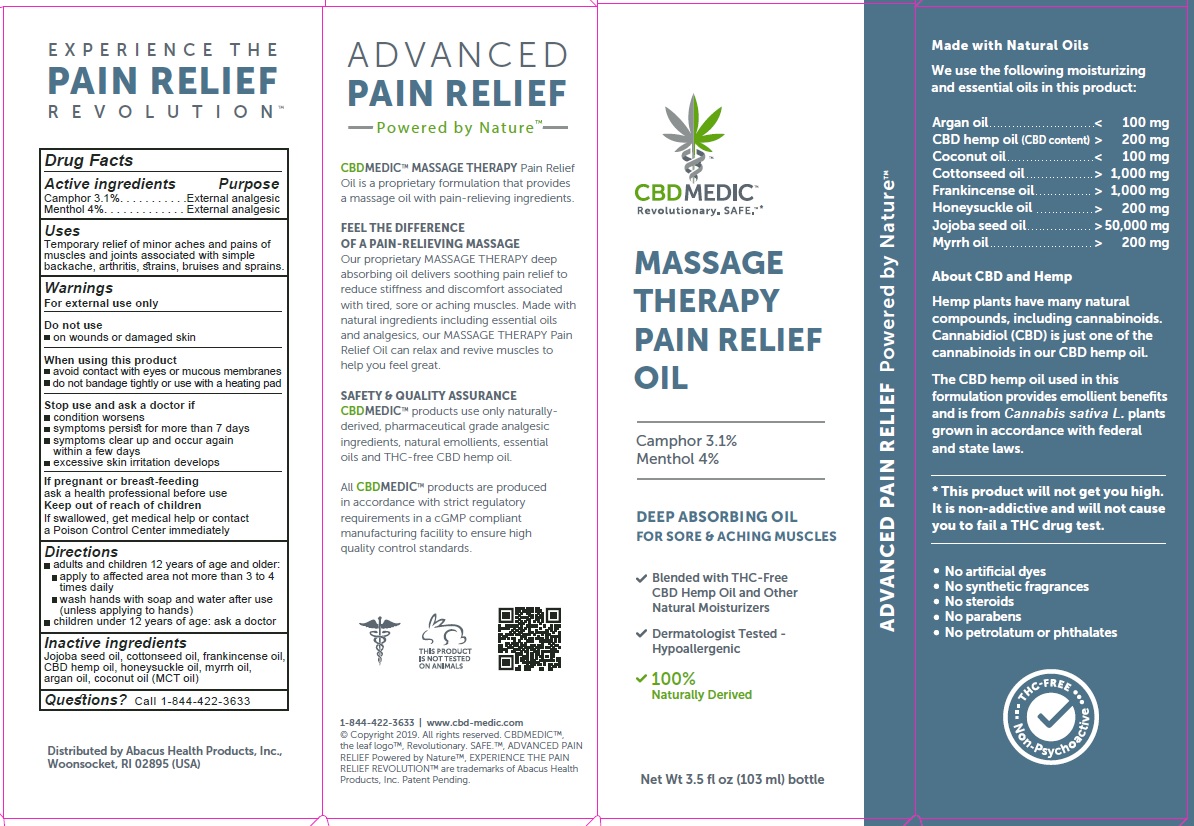 DRUG LABEL: CBDMEDIC Massage Therapy Pain Relief
NDC: 24909-750 | Form: OIL
Manufacturer: AIDANCE SKINCARE & TOPICAL SOLUTIONS, LLC
Category: otc | Type: HUMAN OTC DRUG LABEL
Date: 20191225

ACTIVE INGREDIENTS: CAMPHOR (NATURAL) 31 mg/1 mL; MENTHOL 40 mg/1 mL
INACTIVE INGREDIENTS: ARGAN OIL; COCONUT OIL; COTTONSEED OIL; FRANKINCENSE OIL; HEMP; LONICERA CONFUSA WHOLE; JOJOBA OIL; MYRRH OIL

CBDMEDIC Massage Therapy Pain Relief

Active Ingredients and Purpose

Camphor 3.1%, Menthol 4% (External Analgesics)

Uses

Temporary relief of minor aches and pains of muscles and joints associated with simple backache, arthritis, strains, bruises and sprains

Warnings

For external use only
Do not use on
• wounds or damaged skin
When using this product
• avoid contact with eyes or mucous membranes
• do not bandage tightly or use with a heating pad
Stop use and ask a doctor if
• condition worsens
• symptoms persist for more than 7 days
• symptoms clear up and occur again within a few days
• excessive skin irritation develops
If pregnant or breast-feeding
ask a health professional before use
Keep out of reach of children
If swallowed, get medical help or contact a Poison Control Center immediately

Directions

Adults and children 12 years of age and older:
• apply to affected area not more than 3 to 4 times daily
• wash hands with soap and water after use (unless applying to hands)
Children under 12 years of age: ask a doctor

Inactive ingredients

Jojoba seed oil, cottonseed oil, frankincense oil, CBD hemp oil, honeysuckle oil, myrrh oil, argan oil, coconut oil (MCT oil)

Questions?

Call 1-844-422-3633